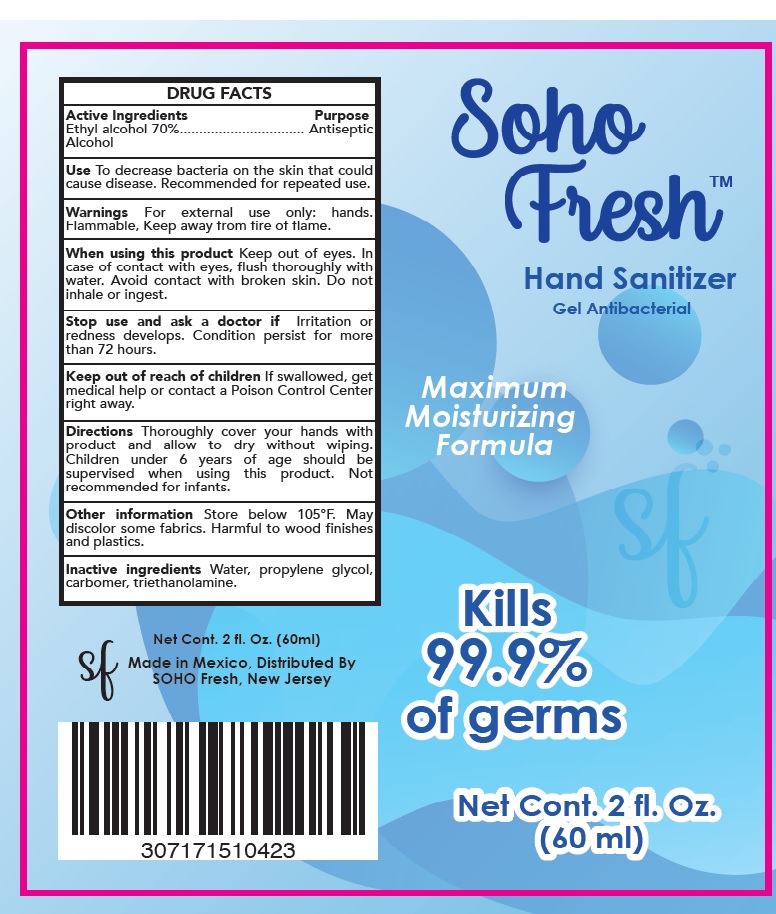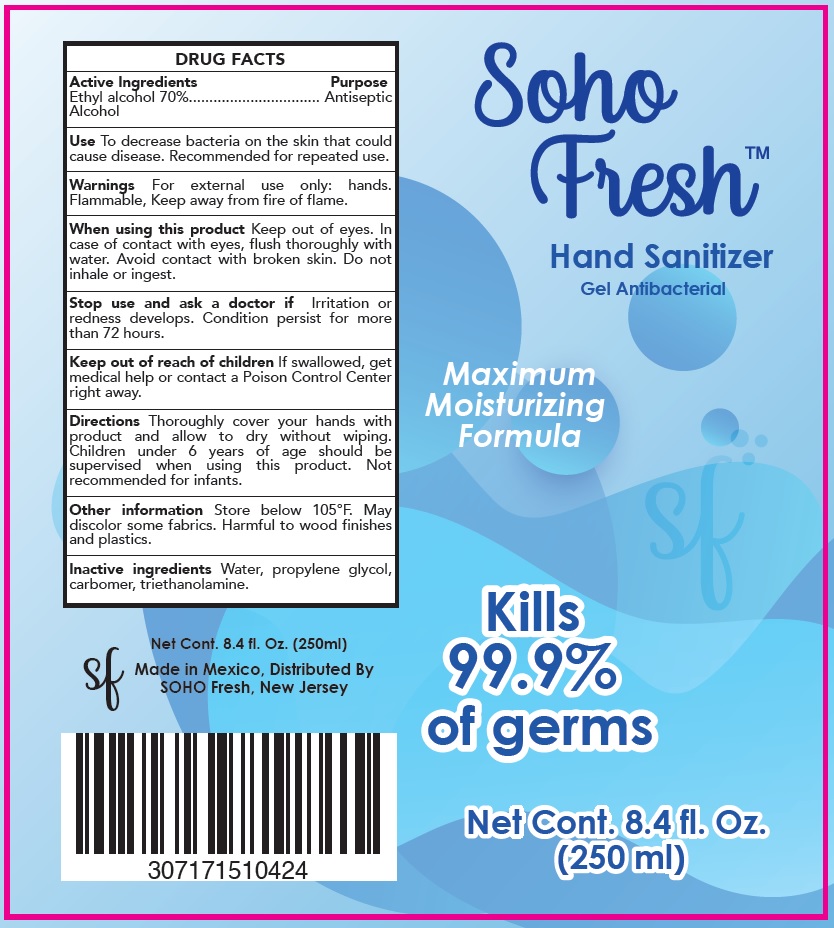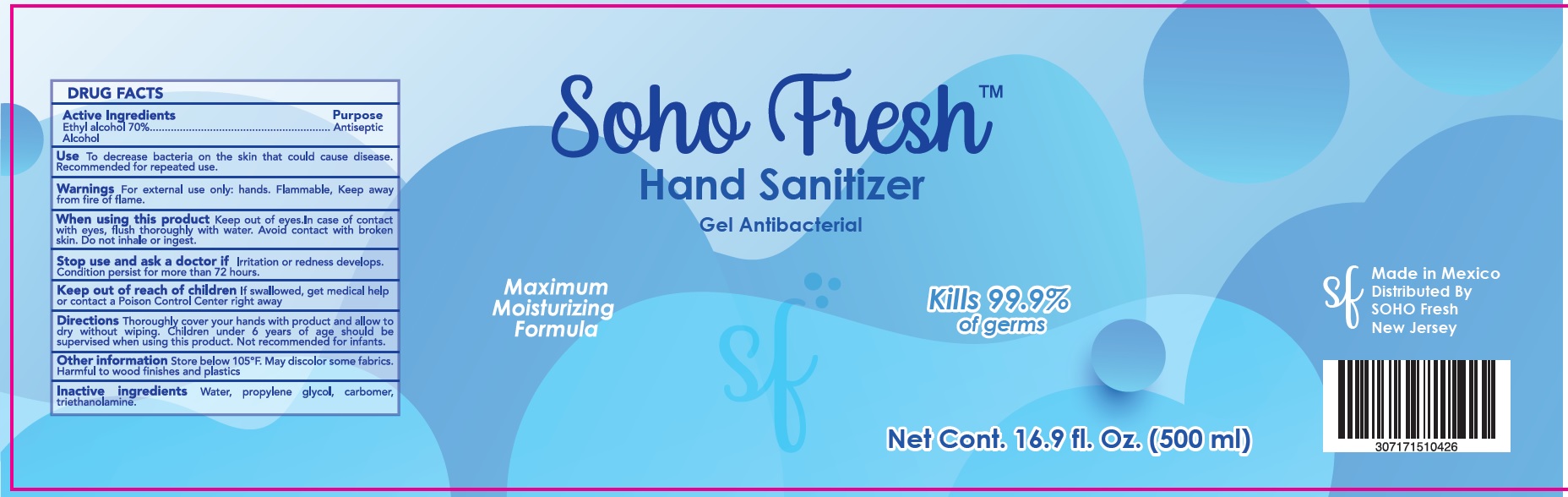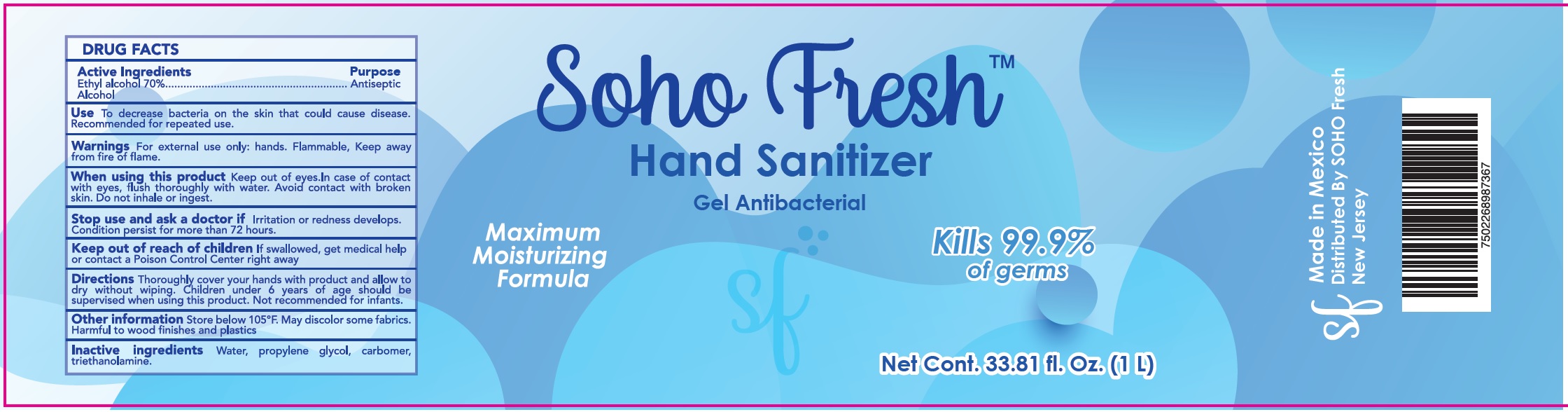 DRUG LABEL: Soho Fresh Hand Sanitizer
NDC: 78533-000 | Form: GEL
Manufacturer: ESSAAR INC.
Category: otc | Type: HUMAN OTC DRUG LABEL
Date: 20200618

ACTIVE INGREDIENTS: ALCOHOL 0.7 1/1 mL
INACTIVE INGREDIENTS: WATER; PROPYLENE GLYCOL; CARBOMER HOMOPOLYMER, UNSPECIFIED TYPE; TROLAMINE

Soho Fresh Hand Sanitizer

Active Ingredients

Ethyl alcohol 70%

Purpose

Antiseptic

Use

To decrease bacteria on the skin that could cause disease. Recommended for repeated use.

Warnings

For external use only: hands. Flammable, Keep away from fire of flame.

When using this product

Keep out of eyes. In case of contact with eyes, flush thoroughly with water. Avoid contact with broken skin. Do not inhale or ingest.

Stop use and ask a doctor if

Irritation or redness develops. Condition persist for more than 72 hours.

Keep out of reach of children

If swallowed, get medical help or contact a Poison Control Center right away.

Directions

Thoroughly cover your hands with product and allow to dry without wiping. Children under 6 years of age should be supervised when using this product. Not recommended for infants.

Other information

Store below 105°F. May discolor some fabrics. Harmful to wood finishes and plastics.

Inactive ingredients

Water, propylene glycol, carbomer, triethanolamine.